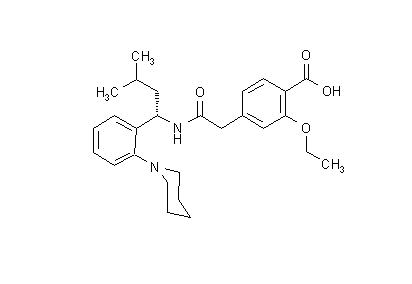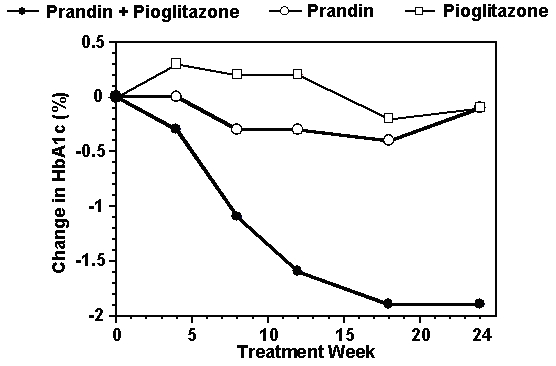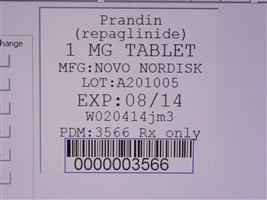 DRUG LABEL: Prandin
NDC: 68151-3566 | Form: TABLET
Manufacturer: Carilion Materials Management
Category: prescription | Type: HUMAN PRESCRIPTION DRUG LABEL
Date: 20160806

ACTIVE INGREDIENTS: REPAGLINIDE 1 mg/1 1

PRANDIN® (repaglinide) Tablets (0.5, 1, and 2 mg)

DESCRIPTION

PRANDIN® (repaglinide) is an oral blood glucose-lowering drug of the meglitinide class used in the management of type 2 diabetes mellitus (also known as non-insulin dependent diabetes mellitus or NIDDM). Repaglinide, S(+)2-ethoxy-4(2((3-methyl-1-(2-(1-piperidinyl) phenyl)-butyl) amino)-2-oxoethyl) benzoic acid, is chemically unrelated to the oral sulfonylurea insulin secretagogues.

The structural formula is as shown below:

Repaglinide is a white to off-white powder with molecular formula C27 H36 N2 O4 and a molecular weight of 452.6. PRANDIN tablets contain 0.5 mg, 1 mg, or 2 mg of repaglinide. In addition each tablet contains the following inactive ingredients: calcium hydrogen phosphate (anhydrous), microcrystalline cellulose, maize starch, polacrilin potassium, povidone, glycerol (85%), magnesium stearate, meglumine, and poloxamer. The 1 mg and 2 mg tablets contain iron oxides (yellow and red, respectively) as coloring agents.

CLINICAL PHARMACOLOGY

Mechanism of Action

Repaglinide lowers blood glucose levels by stimulating the release of insulin from the pancreas. This action is dependent upon functioning beta (ß) cells in the pancreatic islets. Insulin release is glucose-dependent and diminishes at low glucose concentrations.

Repaglinide closes ATP-dependent potassium channels in the ß-cell membrane by binding at characterizable sites. This potassium channel blockade depolarizes the ß-cell, which leads to an opening of calcium channels. The resulting increased calcium influx induces insulin secretion. The ion channel mechanism is highly tissue selective with low affinity for heart and skeletal muscle.

Pharmacokinetics

Absorption: After oral administration, repaglinide is rapidly and completely absorbed from the gastrointestinal tract. After single and multiple oral doses in healthy subjects or in patients, peak plasma drug levels (Cmax) occur within 1 hour (Tmax). Repaglinide is rapidly eliminated from the blood stream with a half-life of approximately 1 hour. The mean absolute bioavailability is 56%. When repaglinide was given with food, the mean Tmax was not changed, but the mean Cmax and AUC (area under the time/plasma concentration curve) were decreased 20% and 12.4%, respectively.

Distribution: After intravenous (IV) dosing in healthy subjects, the volume of distribution at steady state (Vss) was 31 L, and the total body clearance (CL) was 38 L/h. Protein binding and binding to human serum albumin was greater than 98%.

Metabolism: Repaglinide is completely metabolized by oxidative biotransformation and direct conjugation with glucuronic acid after either an IV or oral dose. The major metabolites are an oxidized dicarboxylic acid (M2), the aromatic amine (M1), and the acyl glucuronide (M7). The cytochrome P-450 enzyme system, specifically 2C8 and 3A4, have been shown to be involved in the N-dealkylation of repaglinide to M2 and the further oxidation to M1. Metabolites do not contribute to the glucose-lowering effect of repaglinide.

Repaglinide appears to be a substrate for active hepatic uptake transporter (organic anion transporting protein OATP1B1).

Excretion: Within 96 hours after dosing with ^14C-repaglinide as a single, oral dose, approximately 90% of the radiolabel was recovered in the feces and approximately 8% in the urine. Only 0.1% of the dose is cleared in the urine as parent compound. The major metabolite (M2) accounted for 60% of the administered dose. Less than 2% of parent drug was recovered in feces.

Pharmacokinetic Parameters: The pharmacokinetic parameters of repaglinide obtained from a single-dose, crossover study in healthy subjects and from a multiple-dose, parallel, dose-proportionality (0.5, 1, 2 and 4 mg) study in patients with type 2 diabetes are summarized in the following table:

Parameter | Patients with type 2 diabetes [dosed preprandially with three meals]
Dose; 0.5 mg; 1 mg; 2 mg; 4 mg | AUC0-24 hr Mean ±SD (ng/mL*hr):; 68.9 ± 154.4; 125.8 ± 129.8; 152.4 ± 89.6; 447.4 ± 211.3
Dose; 0.5 mg; 1 mg; 2 mg; 4 mg | Cmax0-5 hr Mean ±SD (ng/mL):; 9.8 ± 10.2; 18.3 ± 9.1; 26.0 ± 13.0; 65.8 ± 30.1
Dose; 0.5 - 4 mg | Tmax0-5 hr Means (SD); 1.0 - 1.4 (0.3 - 0.5) hr
Dose; 0.5 - 4 mg | T½ Means (Ind Range); 1.0 - 1.4 (0.4 - 8.0) hr
Parameter | Healthy Subjects
CL based on i.v. | 38 ± 16 L/hr
Vss based on i.v. | 31 ± 12 L
AbsBio | 56 ± 9%
CL= total body clearance
Vss= volume of distribution at steady state
AbsBio = absolute bioavailability

These data indicate that repaglinide did not accumulate in serum. Clearance of oral repaglinide did not change over the 0.5 - 4 mg dose range, indicating a linear relationship between dose and plasma drug levels.

Variability of Exposure: Repaglinide AUC after multiple doses of 0.25 to 4 mg with each meal varies over a wide range. The intra-individual and inter-individual coefficients of variation were 36% and 69%, respectively. AUC over the therapeutic dose range included 69 to 1005 ng/mL*hr, but AUC exposure up to 5417 ng/mL*hr was reached in dose escalation studies without apparent adverse consequences.

Special Populations

Geriatric: Healthy volunteers were treated with a regimen of 2 mg taken before each of 3 meals. There were no significant differences in repaglinide pharmacokinetics between the group of patients <65 years of age and a comparably sized group of patients ≥65 years of age (See PRECAUTIONS, Geriatric Use).

Pediatric: No studies have been performed in pediatric patients.

Gender: A comparison of pharmacokinetics in males and females showed the AUC over the 0.5 mg to 4 mg dose range to be 15% to 70% higher in females with type 2 diabetes. This difference was not reflected in the frequency of hypoglycemic episodes (male: 16%; female: 17%) or other adverse events. With respect to gender, no change in general dosage recommendation is indicated since dosage for each patient should be individualized to achieve optimal clinical response.

Race: No pharmacokinetic studies to assess the effects of race have been performed, but in a U.S. 1-year study in patients with type 2 diabetes, the blood glucose-lowering effect was comparable between Caucasians (n=297) and African-Americans (n=33). In a U.S. dose-response study, there was no apparent difference in exposure (AUC) between Caucasians (n=74) and Hispanics (n=33).

Drug-Drug Interactions

Drug interaction studies performed in healthy volunteers show that PRANDIN had no clinically relevant effect on the pharmacokinetic properties of digoxin, theophylline, or warfarin. Co-administration of cimetidine with PRANDIN did not significantly alter the absorption and disposition of repaglinide.

Additionally, the following drugs were studied in healthy volunteers with co-administration of PRANDIN. Listed below are the results:

CYP2C8 and CYP3A4 Inhibitors/Inducer

Gemfibrozil and Itraconazole: Co-administration of gemfibrozil (600 mg) and a single dose of 0.25 mg PRANDIN (after 3 days of twice-daily 600 mg gemfibrozil) resulted in an 8.1-fold higher repaglinide AUC and prolonged repaglinide half-life from 1.3 to 3.7 hr. Co-administration with itraconazole and a single dose of 0.25 mg PRANDIN (on the third day of a regimen of 200 mg initial dose, twice-daily 100 mg itraconazole) resulted in a 1.4-fold higher repaglinide AUC. Co-administration of both gemfibrozil and itraconazole with PRANDIN resulted in a 19-fold higher repaglinide AUC and prolonged repaglinide half-life to 6.1 hr. Plasma repaglinide concentration at 7 h increased 28.6-fold with gemfibrozil co-administration and 70.4-fold with the gemfibrozil-itraconazole combination (see CONTRAINDICATIONS, PRECAUTIONS, Drug-Drug Interactions).

Fenofibrate: Co-administration of 200 mg fenofibrate with a single dose of 0.25 mg repaglinide (after 5 days of once daily fenofibrate 200 mg) resulted in unchanged AUC and Cmax values for both drugs.

Ketoconazole: Co-administration of 200 mg ketoconazole and a single dose of 2 mg PRANDIN (after 4 days of once daily ketoconazole 200 mg) resulted in a 15% and 16% increase in repaglinide AUC and Cmax, respectively. The increases were from 20.2 ng/mL to 23.5 ng/mL for Cmax and from 38.9 ng/mL*hr to 44.9 ng/mL*hr for AUC.

Trimethoprim: Co-administration of 160 mg trimethoprim and a single dose of 0.25 mg PRANDIN (after 2 days of twice daily and one dose on the third day of trimethoprim 160 mg) resulted in a 61% and 41% increase in repaglinide AUC and Cmax, respectively. The increase in AUC was from 5.9 ng/mL*hr to 9.6 ng/mL*hr and the increase in Cmax was from 4.7 ng/mL to 6.6 ng/mL.

Cyclosporine: Co-administration of 100 mg cyclosporine with a single dose of 0.25 mg repaglinide (after two 100 mg doses of cyclosporine twelve hours apart) increased the repaglinide (0.25 mg) Cmax 1.8-fold and the AUC 2.5-fold in an interaction study with healthy volunteers (see PRECAUTIONS, Drug-Drug Interactions).

Rifampin: Co-administration of 600 mg rifampin and a single dose of 4 mg PRANDIN (after 6 days of once daily rifampin 600 mg) resulted in a 32% and 26% decrease in repaglinide AUC and Cmax, respectively. The decreases were from 40.4 ng/mL to 29.7 ng/mL for Cmax and from 56.8 ng/mL*hr to 38.7 ng/mL*hr for AUC.

In another study, co-administration of 600 mg rifampin and a single dose of 4 mg PRANDIN (after 6 days of once daily rifampin 600 mg) resulted in a 48% and 17% decrease in repaglinide median AUC and median Cmax respectively. The median decreases were from 54 ng/mL*hr to 28 ng/mL*hr for AUC and from 35 ng/mL to 29 ng/mL for Cmax. PRANDIN administered by itself (after 7 days of once daily rifampin 600 mg) resulted in an 80% and 79% decrease in repaglinide median AUC and Cmax respectively. The decreases were from 54 ng/mL*hr to 11 ng/mL*hr for AUC and from 35 ng/mL to 7.5 ng/mL for Cmax.

Levonorgestrel & Ethinyl Estradiol: Co-administration of a combination tablet of 0.15 mg levonorgestrel and 0.03 mg ethinyl estradiol administered once daily for 21 days with 2 mg PRANDIN administered three times daily (days 1-4) and a single dose on Day 5 resulted in 20% increases in repaglinide, levonorgestrel, and ethinyl estradiol Cmax. The increase in repaglinide Cmax was from 40.5 ng/mL to 47.4 ng/mL. Ethinyl estradiol AUC parameters were increased by 20%, while repaglinide and levonorgestrel AUC values remained unchanged.

Simvastatin: Co-administration of 20 mg simvastatin and a single dose of 2 mg PRANDIN (after 4 days of once daily simvastatin 20 mg and three times daily PRANDIN 2 mg) resulted in a 26% increase in repaglinide Cmax from 23.6 ng/mL to 29.7 ng/mL. AUC was unchanged.

Nifedipine: Co-administration of 10 mg nifedipine with a single dose of 2 mg PRANDIN (after 4 days of three times daily nifedipine 10 mg and three times daily PRANDIN 2 mg) resulted in unchanged AUC and Cmax values for both drugs.

Clarithromycin: Co-administration of 250 mg clarithromycin and a single dose of 0.25 mg PRANDIN (after 4 days of twice daily clarithromycin 250 mg) resulted in a 40% and 67% increase in repaglinide AUC and Cmax, respectively. The increase in AUC was from 5.3 ng/mL*hr to 7.5 ng/mL*hr and the increase in Cmax was from 4.4 ng/mL to 7.3 ng/mL.

Deferasirox: Co-administration of deferasirox (30 mg/kg/day for 4 days) and repaglinide (single dose of 0.5 mg) resulted in an increase in repaglinide systemic exposure (AUC) to 2.3-fold of control and an increase in Cmax of 62% (see PRECAUTIONS, Drug-Drug Interactions).

Renal Insufficiency: Single-dose and steady-state pharmacokinetics of repaglinide were compared between patients with type 2 diabetes and normal renal function (CrCl > 80 mL/min), mild to moderate renal function impairment (CrCl = 40 – 80 mL/min), and severe renal function impairment (CrCl = 20 – 40 mL/min). Both AUC and Cmax of repaglinide were similar in patients with normal and mild to moderately impaired renal function (mean values 56.7 ng/mL*hr vs 57.2 ng/mL*hr and 37.5 ng/mL vs 37.7 ng/mL, respectively.) Patients with severely reduced renal function had elevated mean AUC and Cmax values (98.0 ng/mL*hr and 50.7 ng/mL, respectively), but this study showed only a weak correlation between repaglinide levels and creatinine clearance. Initial dose adjustment does not appear to be necessary for patients with mild to moderate renal dysfunction. However, patients with type 2 diabetes who have severe renal function impairment should initiate PRANDIN therapy with the 0.5 mg dose – subsequently, patients should be carefully titrated. Studies were not conducted in patients with creatinine clearances below 20 mL/min or patients with renal failure requiring hemodialysis.

Hepatic Insufficiency: A single-dose, open-label study was conducted in 12 healthy subjects and 12 patients with chronic liver disease (CLD) classified by Child-Pugh scale and caffeine clearance. Patients with moderate to severe impairment of liver function had higher and more prolonged serum concentrations of both total and unbound repaglinide than healthy subjects (AUChealthy: 91.6 ng/mL*hr; AUCCLD patients: 368.9 ng/mL*hr; Cmax, healthy: 46.7 ng/mL; Cmax, CLD patients: 105.4 ng/mL). AUC was statistically correlated with caffeine clearance. No difference in glucose profiles was observed across patient groups. Patients with impaired liver function may be exposed to higher concentrations of repaglinide and its associated metabolites than would patients with normal liver function receiving usual doses. Therefore, PRANDIN should be used cautiously in patients with impaired liver function. Longer intervals between dose adjustments should be utilized to allow full assessment of response.

Clinical Trials

Monotherapy Trials

A four-week, double-blind, placebo-controlled dose-response trial was conducted in 138 patients with type 2 diabetes using doses ranging from 0.25 to 4 mg taken with each of three meals. PRANDIN therapy resulted in dose-proportional glucose lowering over the full dose range. Plasma insulin levels increased after meals and reverted toward baseline before the next meal. Most of the fasting blood glucose-lowering effect was demonstrated within 1-2 weeks.

In a double-blind, placebo-controlled, 3-month dose titration study, PRANDIN or placebo doses for each patient were increased weekly from 0.25 mg through 0.5, 1, and 2 mg, to a maximum of 4 mg, until a fasting plasma glucose (FPG) level <160 mg/dL was achieved or the maximum dose reached. The dose that achieved the targeted control or the maximum dose was continued to end of study. FPG and 2-hour post-prandial glucose (PPG) increased in patients receiving placebo and decreased in patients treated with repaglinide. Differences between the repaglinide- and placebo-treated groups were -61 mg/dL (FPG) and -104 mg/dL (PPG). The between-group change in HbA1c, which reflects long-term glycemic control, was 1.7% units.

PRANDIN vs. Placebo Treatment: Mean FPG, PPG, and HbA1c Changes from baseline after 3 months of treatment:
 | FPG (mg/dL) |  | PPG (mg/dL) |  | HbA1c (%)
 | PL | R | PL | R | PL | R
Baseline | 215.3 | 220.2 | 245.2 | 261.7 | 8.1 | 8.5
Change from Baseline; (at last visit) | 30.3 | -31.0 [p < 0.05 for between group difference] | 56.5 | -47.6 | 1.1 | -0.6
FPG = fasting plasma glucose
PPG = post-prandial glucose
PL = placebo (N=33)
R = repaglinide (N=66)

Another double-blind, placebo-controlled trial was carried out in 362 patients treated for 24 weeks. The efficacy of 1 and 4 mg preprandial doses was demonstrated by lowering of fasting blood glucose and by HbA1c at the end of the study. HbA1c for the PRANDIN- treated groups (1 and 4 mg groups combined) at the end of the study was decreased compared to the placebo-treated group in previously naïve patients and in patients previously treated with oral hypoglycemic agents by 2.1% units and 1.7% units, respectively. In this fixed-dose trial, patients who were naïve to oral hypoglycemic agent therapy and patients in relatively good glycemic control at baseline (HbA1c below 8%) showed greater blood glucose-lowering including a higher frequency of hypoglycemia. Patients who were previously treated and who had baseline HbA1c ≥ 8% reported hypoglycemia at the same rate as patients randomized to placebo. There was no average gain in body weight when patients previously treated with oral hypoglycemic agents were switched to PRANDIN. The average weight gain in patients treated with PRANDIN and not previously treated with sulfonylurea drugs was 3.3%.

The dosing of PRANDIN relative to meal-related insulin release was studied in three trials including 58 patients. Glycemic control was maintained during a period in which the meal and dosing pattern was varied (2, 3 or 4 meals per day; before meals x 2, 3, or 4) compared with a period of 3 regular meals and 3 doses per day (before meals x 3). It was also shown that PRANDIN can be administered at the start of a meal, 15 minutes before, or 30 minutes before the meal with the same blood glucose-lowering effect.

PRANDIN was compared to other insulin secretagogues in 1-year controlled trials to demonstrate comparability of efficacy and safety. Hypoglycemia was reported in 16% of 1228 PRANDIN patients, 20% of 417 glyburide patients, and 19% of 81 glipizide patients. Of PRANDIN-treated patients with symptomatic hypoglycemia, none developed coma or required hospitalization.

Combination Trials

PRANDIN was studied in combination with metformin in 83 patients not satisfactorily controlled on exercise, diet, and metformin alone. PRANDIN dosage was titrated for 4 to 8 weeks, followed by a 3-month maintenance period. Combination therapy with PRANDIN and metformin resulted in significantly greater improvement in glycemic control as compared to repaglinide or metformin monotherapy. HbA1c was improved by 1% unit and FPG decreased by an additional 35 mg/dL. In this study where metformin dosage was kept constant, the combination therapy of PRANDIN and metformin showed dose-sparing effects with respect to PRANDIN. The greater efficacy response of the combination group was achieved at a lower daily repaglinide dosage than in the PRANDIN monotherapy group (see Table).

PRANDIN and Metformin Therapy: Mean Changes from Baseline in Glycemic Parameters and Weight after 4 to 5 Months of Treatment [based on intent-to-treat analysis]
 | PRANDIN | Combination | Metformin
N | 28 | 27 | 27
Median Final Dose; (mg/day) | 12 | 6 (PRANDIN); 1500 (metformin) | 1500
HbA1c (% units) | -0.38 | -1.41 [p < 0.05, for pairwise comparisons with PRANDIN and metformin.] | -0.33
FPG (mg/dL) | 8.8 | -39.2 | -4.5
Weight (kg) | 3.0 | 2.4 [p < 0.05, for pairwise comparison with metformin.] | -0.90

A combination therapy regimen of PRANDIN and pioglitazone was compared to monotherapy with either agent alone in a 24-week trial that enrolled 246 patients previously treated with sulfonylurea or metformin monotherapy (HbA1c > 7.0%). Numbers of patients treated were: PRANDIN (N = 61), pioglitazone (N = 62), combination (N = 123). PRANDIN dosage was titrated during the first 12 weeks, followed by a 12-week maintenance period. Combination therapy resulted in significantly greater improvement in glycemic control as compared to monotherapy (figure below). The changes from baseline for completers in FPG (mg/dL) and HbA1c (%), respectively were: -39.8 and -0.1 for PRANDIN, -35.3 and -0.1 for pioglitazone and -92.4 and -1.9 for the combination. In this study where pioglitazone dosage was kept constant, the combination therapy group showed dose-sparing effects with respect to PRANDIN (see figure legend). The greater efficacy response of the combination group was achieved at a lower daily repaglinide dosage than in the PRANDIN monotherapy group. Mean weight increases associated with combination, PRANDIN and pioglitazone therapy were 5.5 kg, 0.3 kg, and 2.0 kg respectively.

HbA1c Values from PRANDIN / Pioglitazone Combination Study

HbA1c values by study week for patients who completed study (combination, N = 101; PRANDIN, N = 35, pioglitazone, N = 26).

Subjects with FPG above 270 mg/dL were withdrawn from the study.

Pioglitazone dose: fixed at 30 mg/day; PRANDIN median final dose: 6 mg/day for combination and 10 mg/day for monotherapy.

A combination therapy regimen of PRANDIN and rosiglitazone was compared to monotherapy with either agent alone in a 24-week trial that enrolled 252 patients previously treated with sulfonylurea or metformin (HbA1c > 7.0%). Combination therapy resulted in significantly greater improvement in glycemic control as compared to monotherapy (table below). The glycemic effects of the combination therapy were dose-sparing with respect to both total daily PRANDIN dosage and total daily rosiglitazone dosage (see table legend). A greater efficacy response of the combination therapy group was achieved with half the median daily dose of PRANDIN and rosiglitazone, as compared to the respective monotherapy groups. Mean weight change associated with combination therapy was greater than that of PRANDIN monotherapy.

Mean Changes from Baseline in Glycemic Parameters and Weight in a 24-Week PRANDIN/Rosiglitazone Combination Study [based on intent-to-treat analysis]
 | PRANDIN | Combination | Rosiglitazone
N | 63 | 127 | 62
HbA1c (%)
Baseline | 9.3 | 9.1 | 9.0
Change by 24 weeks | -0.17 | -1.43 [p-value ≤ 0.001 for comparison to either monotherapy] | -0.56
FPG (mg/dL)
Baseline | 269 | 257 | 252
Change by 24 weeks | -54 | -94 | -67
Change in Weight (kg) | +1.3 | +4.5 [p-value < 0.001 for comparison to PRANDIN] | +3.3
Final median doses: rosiglitazone - 4 mg/day for combination and 8 mg/day for monotherapy; PRANDIN - 6 mg/day for combination and 12 mg/day for monotherapy

INDICATIONS AND USAGE

PRANDIN is indicated as an adjunct to diet and exercise to improve glycemic control in adults with type 2 diabetes mellitus.

CONTRAINDICATIONS

PRANDIN is contraindicated in patients with:

1. Diabetic ketoacidosis, with or without coma. This condition should be treated with insulin.
2. Type 1 diabetes.
3. Co-administration of gemfibrozil.
4. Known hypersensitivity to the drug or its inactive ingredients.

PRECAUTIONS

General:

PRANDIN is not indicated for use in combination with NPH-insulin (See ADVERSE REACTIONS, Cardiovascular Events).

Macrovascular Outcomes:

There have been no clinical studies establishing conclusive evidence of macrovascular risk reduction with PRANDIN or any other anti-diabetic drug.

Hypoglycemia: All oral blood glucose-lowering drugs including repaglinide are capable of producing hypoglycemia. Proper patient selection, dosage, and instructions to the patients are important to avoid hypoglycemic episodes. Hepatic insufficiency may cause elevated repaglinide blood levels and may diminish gluconeogenic capacity, both of which increase the risk of serious hypoglycemia. Elderly, debilitated, or malnourished patients, and those with adrenal, pituitary, hepatic, or severe renal insufficiency may be particularly susceptible to the hypoglycemic action of glucose-lowering drugs.

Hypoglycemia may be difficult to recognize in the elderly and in people taking beta-adrenergic blocking drugs. Hypoglycemia is more likely to occur when caloric intake is deficient, after severe or prolonged exercise, when alcohol is ingested, or when more than one glucose-lowering drug is used.

The frequency of hypoglycemia is greater in patients with type 2 diabetes who have not been previously treated with oral blood glucose-lowering drugs (naïve) or whose HbA1c is less than 8%. PRANDIN should be administered with meals to lessen the risk of hypoglycemia.

Loss of Control of Blood Glucose: When a patient stabilized on any diabetic regimen is exposed to stress such as fever, trauma, infection, or surgery, a loss of glycemic control may occur. At such times, it may be necessary to discontinue PRANDIN and administer insulin. The effectiveness of any hypoglycemic drug in lowering blood glucose to a desired level decreases in many patients over a period of time, which may be due to progression of the severity of diabetes or to diminished responsiveness to the drug. This phenomenon is known as secondary failure, to distinguish it from primary failure in which the drug is ineffective in an individual patient when the drug is first given. Adequate adjustment of dose and adherence to diet should be assessed before classifying a patient as a secondary failure.

Information for Patients

Patients should be informed of the potential risks and advantages of PRANDIN and of alternative modes of therapy. They should also be informed about the importance of adherence to dietary instructions, of a regular exercise program, and of regular testing of blood glucose and HbA1c. The risks of hypoglycemia, its symptoms and treatment, and conditions that predispose to its development and concomitant administration of other glucose-lowering drugs should be explained to patients and responsible family members. Primary and secondary failure should also be explained.

Patients should be instructed to take PRANDIN before meals (2, 3, or 4 times a day preprandially). Doses are usually taken within 15 minutes of the meal but time may vary from immediately preceding the meal to as long as 30 minutes before the meal. Patients who skip a meal (or add an extra meal) should be instructed to skip (or add) a dose for that meal.

Laboratory Tests

Response to all diabetic therapies should be monitored by periodic measurements of fasting blood glucose and glycosylated hemoglobin levels with a goal of decreasing these levels towards the normal range. During dose adjustment, fasting glucose can be used to determine the therapeutic response. Thereafter, both glucose and glycosylated hemoglobin should be monitored. Glycosylated hemoglobin may be especially useful for evaluating long-term glycemic control. Postprandial glucose level testing may be clinically helpful in patients whose pre-meal blood glucose levels are satisfactory but whose overall glycemic control (HbA1c) is inadequate.

Drug-Drug Interactions

In vitro data indicate that PRANDIN is metabolized by cytochrome P450 enzymes 2C8 and 3A4. Consequently, repaglinide metabolism may be altered by drugs which influence these cytochrome P450 enzyme systems via induction and inhibition. Caution should therefore be used in patients who are on PRANDIN and taking inhibitors and/or inducers of CYP2C8 and CYP3A4. The effect may be very significant if both enzymes are inhibited at the same time resulting in a substantial increase in repaglinide plasma concentrations. Drugs that are known to inhibit CYP3A4 include antifungal agents like ketoconazole, itraconazole, and antibacterial agents like erythromycin. Drugs that are known to inhibit CYP2C8 include agents like trimethoprim, gemfibrozil and montelukast. Drugs that induce the CYP3A4 and/or 2C8 enzyme systems include rifampin, barbiturates, and carbamezapine. See CLINICAL PHARMACOLOGY section, Drug-Drug Interactions.

Repaglinide appears to be a substrate for active hepatic uptake transporter (organic anion transporting protein OATP1B1). Drugs that inhibit OATP1B1 (e.g. cyclosporine) may likewise have the potential to increase plasma concentrations of repaglinide. See CLINICAL PHARMACOLOGY section, Drug-Drug Interactions.

In vivo data from a study that evaluated the co-administration of a cytochrome P450 enzyme 3A4 inhibitor, clarithromycin, with PRANDIN resulted in a clinically significant increase in repaglinide plasma levels. In addition, an increase in repaglinide plasma levels was observed in studies that evaluated the co-administration of PRANDIN with trimethoprim and PRANDIN with deferasirox, both cytochrome P-450 enzyme 2C8 inhibitors. These increases in repaglinide plasma levels may necessitate a PRANDIN dose adjustment. See CLINICAL PHARMACOLOGY section, Drug-Drug Interactions.

Gemfibrozil significantly increased PRANDIN exposure. Therefore, patients should not take PRANDIN with gemfibrozil. See CLINICAL PHARMACOLOGY section, Drug-Drug Interactions, and CONTRAINDICATIONS.

The hypoglycemic action of oral blood glucose-lowering agents may be potentiated by certain drugs including nonsteroidal anti-inflammatory agents and other drugs that are highly protein bound, salicylates, sulfonamides, cyclosporine, chloramphenicol, coumarins, probenecid, monoamine oxidase inhibitors, and beta adrenergic blocking agents. When such drugs are administered to a patient receiving oral blood glucose-lowering agents, the patient should be observed closely for hypoglycemia. When such drugs are withdrawn from a patient receiving oral blood glucose-lowering agents, the patient should be observed closely for loss of glycemic control.

Certain drugs tend to produce hyperglycemia and may lead to loss of glycemic control. These drugs include the thiazides and other diuretics, corticosteroids, phenothiazines, thyroid products, estrogens, oral contraceptives, phenytoin, nicotinic acid, sympathomimetics, calcium channel blocking drugs, and isoniazid. When these drugs are administered to a patient receiving oral blood glucose-lowering agents, the patient should be observed for loss of glycemic control. When these drugs are withdrawn from a patient receiving oral blood glucose-lowering agents, the patient should be observed closely for hypoglycemia.

Carcinogenesis, Mutagenesis, and Impairment of Fertility

Long-term carcinogenicity studies were performed for 104 weeks at doses up to and including 120 mg/kg body weight/day (rats) and 500 mg/kg body weight/day (mice) or approximately 60 and 125 times clinical exposure, respectively, on a mg/m^2 basis. No evidence of carcinogenicity was found in mice or female rats. In male rats, there was an increased incidence of benign adenomas of the thyroid and liver. The relevance of these findings to humans is unclear. The no-effect doses for these observations in male rats were 30 mg/kg body weight/day for thyroid tumors and 60 mg/kg body weight/day for liver tumors, which are over 15 and 30 times, respectively, clinical exposure on a mg/m^2 basis.

Repaglinide was non-genotoxic in a battery of in vivo and in vitro studies: Bacterial mutagenesis (Ames test), in vitro forward cell mutation assay in V79 cells (HGPRT), in vitro chromosomal aberration assay in human lymphocytes, unscheduled and replicating DNA synthesis in rat liver, and in vivo mouse and rat micronucleus tests.

Fertility of male and female rats was unaffected by repaglinide administration at doses up to 80 mg/kg body weight/day (females) and 300 mg/kg body weight/day (males); over 40 times clinical exposure on a mg/m^2 basis.

Pregnancy

Pregnancy category C

Teratogenic Effects: Safety in pregnant women has not been established. Repaglinide was not teratogenic in rats or rabbits at doses 40 times (rats) and approximately 0.8 times (rabbit) clinical exposure (on a mg/m^2 basis) throughout pregnancy. Because animal reproduction studies are not always predictive of human response, PRANDIN should be used during pregnancy only if it is clearly needed.

Because recent information suggests that abnormal blood glucose levels during pregnancy are associated with a higher incidence of congenital abnormalities, many experts recommend that insulin be used during pregnancy to maintain blood glucose levels as close to normal as possible.

Nonteratogenic Effects: Offspring of rat dams exposed to repaglinide at 15 times clinical exposure on a mg/m^2 basis during days 17 to 22 of gestation and during lactation developed nonteratogenic skeletal deformities consisting of shortening, thickening, and bending of the humerus during the postnatal period. This effect was not seen at doses up to 2.5 times clinical exposure (on a mg/m^2 basis) on days 1 to 22 of pregnancy or at higher doses given during days 1 to 16 of pregnancy. Relevant human exposure has not occurred to date and therefore the safety of PRANDIN administration throughout pregnancy or lactation cannot be established.

Nursing Mothers

In rat reproduction studies, measurable levels of repaglinide were detected in the breast milk of the dams and lowered blood glucose levels were observed in the pups. Cross fostering studies indicated that skeletal changes (see Nonteratogenic Effects) could be induced in control pups nursed by treated dams, although this occurred to a lesser degree than those pups treated in utero. Although it is not known whether repaglinide is excreted in human milk some oral agents are known to be excreted by this route. Because the potential for hypoglycemia in nursing infants may exist, and because of the effects on nursing animals, a decision should be made as to whether PRANDIN should be discontinued in nursing mothers, or if mothers should discontinue nursing. If PRANDIN is discontinued and if diet alone is inadequate for controlling blood glucose, insulin therapy should be considered.

Pediatric Use

No studies have been performed in pediatric patients.

Geriatric Use

In repaglinide clinical studies of 24 weeks or greater duration, 415 patients were over 65 years of age. In one-year, active-controlled trials, no differences were seen in effectiveness or adverse events between these subjects and those less than 65 other than the expected age-related increase in cardiovascular events observed for PRANDIN and comparator drugs. There was no increase in frequency or severity of hypoglycemia in older subjects. Other reported clinical experience has not identified differences in responses between the elderly and younger patients, but greater sensitivity of some older individuals to PRANDIN therapy cannot be ruled out.

ADVERSE REACTIONS

Hypoglycemia: See PRECAUTIONS and OVERDOSAGE sections.

PRANDIN has been administered to 2931 individuals during clinical trials. Approximately 1500 of these individuals with type 2 diabetes have been treated for at least 3 months, 1000 for at least 6 months, and 800 for at least 1 year. The majority of these individuals (1228) received PRANDIN in one of five 1-year, active-controlled trials. The comparator drugs in these 1-year trials were oral sulfonylurea drugs (SU) including glyburide and glipizide. Over one year, 13% of PRANDIN patients were discontinued due to adverse events, as were 14% of SU patients. The most common adverse events leading to withdrawal were hyperglycemia, hypoglycemia, and related symptoms (see PRECAUTIONS). Mild or moderate hypoglycemia occurred in 16% of PRANDIN patients, 20% of glyburide patients, and 19% of glipizide patients.

The table below lists common adverse events for PRANDIN patients compared to both placebo (in trials 12 to 24 weeks duration) and to glyburide and glipizide in one year trials. The adverse event profile of PRANDIN was generally comparable to that for sulfonylurea drugs (SU).

Commonly Reported Adverse Events (% of Patients) [Events ≥ 2% for the PRANDIN group in the placebo-controlled studies and ≥ events in the placebo group]
EVENT | PRANDIN | PLACEBO | PRANDIN | SU
EVENT | N = 352 | N = 108 | N = 1228 | N = 498
EVENT | Placebo controlled studies |  | Active controlled studies
Metabolic
Hypoglycemia | 31 [See trial description in CLINICAL PHARMACOLOGY, Clinical Trials] | 7 | 16 | 20
Respiratory
URI | 16 | 8 | 10 | 10
Sinusitis | 6 | 2 | 3 | 4
Rhinitis | 3 | 3 | 7 | 8
Bronchitis | 2 | 1 | 6 | 7
Gastrointestinal
Nausea | 5 | 5 | 3 | 2
Diarrhea | 5 | 2 | 4 | 6
Constipation | 3 | 2 | 2 | 3
Vomiting | 3 | 3 | 2 | 1
Dyspepsia | 2 | 2 | 4 | 2
Musculoskeletal
Arthralgia | 6 | 3 | 3 | 4
Back Pain | 5 | 4 | 6 | 7
Other
Headache | 11 | 10 | 9 | 8
Paresthesia | 3 | 3 | 2 | 1
Chest pain | 3 | 1 | 2 | 1
Urinary tract infection | 2 | 1 | 3 | 3
Tooth disorder | 2 | 0 | <1 | <1
Allergy | 2 | 0 | 1 | <1

Cardiovascular Events

In one-year trials comparing PRANDIN to sulfonylurea drugs, the incidence of angina was comparable (1.8%) for both treatments, with an incidence of chest pain of 1.8% for PRANDIN and 1.0% for sulfonylureas. The incidence of other selected cardiovascular events (hypertension, abnormal EKG, myocardial infarction, arrhythmias, and palpitations) was ≤ 1% and not different between PRANDIN and the comparator drugs.

The incidence of total serious cardiovascular adverse events, including ischemia, was higher for repaglinide (4%) than for sulfonylurea drugs (3%) in controlled comparator clinical trials. In 1-year controlled trials, PRANDIN treatment was not associated with excess mortality when compared to the rates observed with other oral hypoglycemic agent therapies.

Summary of Serious Cardiovascular Events (% of total patients with events) in Trials Comparing PRANDIN to Sulfonylureas
 | PRANDIN | SU [glyburide and glipizide]
Total Exposed | 1228 | 498
Serious CV Events | 4% | 3%
Cardiac Ischemic Events | 2% | 2%
Deaths due to CV Events | 0.5% | 0.4%

Seven controlled clinical trials included PRANDIN combination therapy with NPH-insulin (n=431), insulin formulations alone (n=388) or other combinations (sulfonylurea plus NPH-insulin or PRANDIN plus metformin) (n=120). There were six serious adverse events of myocardial ischemia in patients treated with PRANDIN plus NPH-insulin from two studies, and one event in patients using insulin formulations alone from another study.

Infrequent Adverse Events (<1% of Patients)

Less common adverse clinical or laboratory events observed in clinical trials included elevated liver enzymes, thrombocytopenia, leukopenia, and anaphylactoid reactions.

Although no causal relationship with repaglinide has been established, postmarketing experience includes reports of the following rare adverse events: alopecia, hemolytic anemia, pancreatitis, Stevens-Johnson Syndrome, and severe hepatic dysfunction including jaundice and hepatitis.

Combination Therapy with Thiazolidinediones

During 24-week treatment clinical trials of PRANDIN-rosiglitazone or PRANDIN-pioglitazone combination therapy (a total of 250 patients in combination therapy), hypoglycemia (blood glucose < 50 mg/dL) occurred in 7% of combination therapy patients in comparison to 7% for PRANDIN monotherapy, and 2% for thiazolidinedione monotherapy.

Peripheral edema was reported in 12 out of 250 PRANDIN-thiazolidinedione combination therapy patients and 3 out of 124 thiazolidinedione monotherapy patients, with no cases reported in these trials for PRANDIN monotherapy. When corrected for dropout rates of the treatment groups, the percentage of patients having events of peripheral edema per 24 weeks of treatment were 5% for PRANDIN-thiazolidinedione combination therapy, and 4% for thiazolidinedione monotherapy. There were reports in 2 of 250 patients (0.8%) treated with PRANDIN-thiazolidinedione therapy of episodes of edema with congestive heart failure. Both patients had a prior history of coronary artery disease and recovered after treatment with diuretic agents. No comparable cases in the monotherapy treatment groups were reported.

Mean change in weight from baseline was +4.9 kg for PRANDIN-thiazolidinedione therapy. There were no patients on PRANDIN-thiazolidinedione combination therapy who had elevations of liver transaminases (defined as 3 times the upper limit of normal levels).

OVERDOSAGE

In a clinical trial, patients received increasing doses of PRANDIN up to 80 mg a day for 14 days. There were few adverse effects other than those associated with the intended effect of lowering blood glucose. Hypoglycemia did not occur when meals were given with these high doses. Hypoglycemic symptoms without loss of consciousness or neurologic findings should be treated aggressively with oral glucose and adjustments in drug dosage and/or meal patterns. Close monitoring may continue until the physician is assured that the patient is out of danger. Patients should be closely monitored for a minimum of 24 to 48 hours, since hypoglycemia may recur after apparent clinical recovery. There is no evidence that repaglinide is dialyzable using hemodialysis.

Severe hypoglycemic reactions with coma, seizure, or other neurological impairment occur infrequently, but constitute medical emergencies requiring immediate hospitalization. If hypoglycemic coma is diagnosed or suspected, the patient should be given a rapid intravenous injection of concentrated (50%) glucose solution. This should be followed by a continuous infusion of more dilute (10%) glucose solution at a rate that will maintain the blood glucose at a level above 100 mg/dL.

DOSAGE AND ADMINISTRATION

There is no fixed dosage regimen for the management of type 2 diabetes with PRANDIN.

The patient's blood glucose should be monitored periodically to determine the minimum effective dose for the patient; to detect primary failure, i.e., inadequate lowering of blood glucose at the maximum recommended dose of medication; and to detect secondary failure, i.e., loss of an adequate blood glucose-lowering response after an initial period of effectiveness. Glycosylated hemoglobin levels are of value in monitoring the patient's longer term response to therapy.

Short-term administration of PRANDIN may be sufficient during periods of transient loss of control in patients usually well controlled on diet.

PRANDIN doses are usually taken within 15 minutes of the meal but time may vary from immediately preceding the meal to as long as 30 minutes before the meal.

Starting Dose

For patients not previously treated or whose HbA1c is < 8%, the starting dose should be 0.5 mg with each meal. For patients previously treated with blood glucose-lowering drugs and whose HbA1c is ≥ 8%, the initial dose is 1 or 2 mg with each meal preprandially (see previous paragraph).

Dose Adjustment

Dosing adjustments should be determined by blood glucose response, usually fasting blood glucose. Postprandial glucose levels testing may be clinically helpful in patients whose pre-meal blood glucose levels are satisfactory but whose overall glycemic control (HbA1c) is inadequate. The preprandial dose should be doubled up to 4 mg with each meal until satisfactory blood glucose response is achieved. At least one week should elapse to assess response after each dose adjustment.

The recommended dose range is 0.5 mg to 4 mg taken with meals. PRANDIN may be dosed preprandially 2, 3, or 4 times a day in response to changes in the patient’s meal pattern. The maximum recommended daily dose is 16 mg.

Patient Management

Long-term efficacy should be monitored by measurement of HbA1c levels approximately every 3 months. Failure to follow an appropriate dosage regimen may precipitate hypoglycemia or hyperglycemia. Patients who do not adhere to their prescribed dietary and drug regimen are more prone to exhibit unsatisfactory response to therapy including hypoglycemia. When hypoglycemia occurs in patients taking a combination of PRANDIN and a thiazolidinedione or PRANDIN and metformin, the dose of PRANDIN should be reduced.

Patients Receiving Other Oral Hypoglycemic Agents

When PRANDIN is used to replace therapy with other oral hypoglycemic agents, PRANDIN may be started on the day after the final dose is given. Patients should then be observed carefully for hypoglycemia due to potential overlapping of drug effects. When transferred from longer half-life sulfonylurea agents (e.g., chlorpropamide) to repaglinide, close monitoring may be indicated for up to one week or longer.

Combination Therapy

If PRANDIN monotherapy does not result in adequate glycemic control, metformin or a thiazolidinedione may be added. If metformin or thiazolidinedione monotherapy does not provide adequate control, PRANDIN may be added. The starting dose and dose adjustments for PRANDIN combination therapy is the same as for PRANDIN monotherapy. The dose of each drug should be carefully adjusted to determine the minimal dose required to achieve the desired pharmacologic effect. Failure to do so could result in an increase in the incidence of hypoglycemic episodes. Appropriate monitoring of FPG and HbA1c measurements should be used to ensure that the patient is not subjected to excessive drug exposure or increased probability of secondary drug failure.

HOW SUPPLIED

Product: 68151-3566

NDC: 68151-3566-8 1 TABLET in a PACKAGE